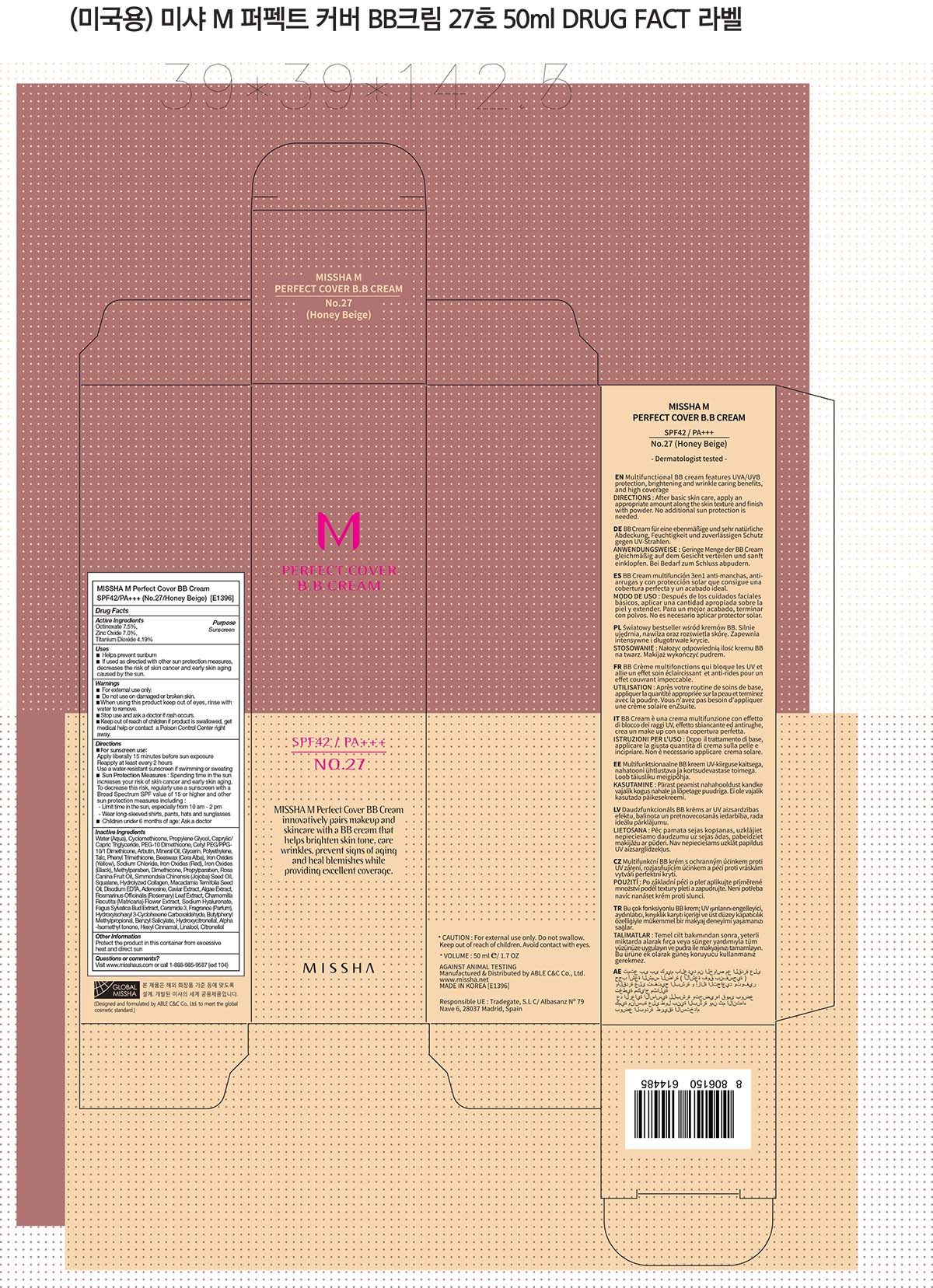 DRUG LABEL: MISSHA M Perfect Cover BB No 27
NDC: 13733-170 | Form: CREAM
Manufacturer: Able C&C Co., Ltd.
Category: otc | Type: HUMAN OTC DRUG LABEL
Date: 20241205

ACTIVE INGREDIENTS: ZINC OXIDE 3.5 g/50 mL; TITANIUM DIOXIDE 2.09 g/50 mL; OCTINOXATE 3.75 g/50 mL
INACTIVE INGREDIENTS: MEDIUM-CHAIN TRIGLYCERIDES; PEG-10 DIMETHICONE (600 CST); GLYCERIN; MINERAL OIL; FERRIC OXIDE YELLOW; YELLOW WAX; DIMETHICONE; ROSEMARY; CERAMIDE AP; CYCLOMETHICONE; WATER; ABRONIA VILLOSA LEAF; HIGH DENSITY POLYETHYLENE; PROPYLENE GLYCOL; TALC; FERROSOFERRIC OXIDE; METHYLPARABEN; PROPYLPARABEN; CYCLOMETHICONE 4; LAMINARIA HYPERBOREA; CHAMOMILE FLOWER OIL; FAGUS SYLVATICA FLOWER BUD; CAPRYLYL GLYCOL; TOCOPHEROL; TROPOLONE; TRIS(TRIMETHYLSILOXY)PHENYLSILANE; SODIUM CHLORIDE; FERRIC OXIDE RED; SQUALANE; MACADAMIA OIL; JOJOBA OIL; EDETATE DISODIUM ANHYDROUS; ADENOSINE; BUTYLENE GLYCOL; BENZYL ALCOHOL; 1,2-HEXANEDIOL; CAPRYLHYDROXAMIC ACID; BENZOIC ACID; HYALURONATE SODIUM; PHENOXYETHANOL; ARBUTIN

MISSHA M Perfect Cover BB No 27

Active Ingredients

Active Ingredients: Zinc Oxide 7%, Titanium Dioxide 4.19%, Ethylhexyl Methoxycinnamate 7.5%

Purpose

Sunscreen

Uses

- helps prevent sunburn
- if used as directed with other sun protection measures (see Directions), decreases the risk of skin cancer and early skin aging caused by the sun

Directions

- apply liberally 15 minutes before sun exposure
- reapply at least every 2 hours
- use a water-resistant sunscreen if swimming or sweating

Sun protection Measures. Spending time in the sun increases your risk of skin cancer and early skin aging. To decrease this risk, regulary use a sunscreen with SPF value of 15 or higher and other sun protection measures including:

- limit time in the sun, especially from 10 a.m. - 2 p.m.
- wear long-sleeved shirts, pants, hats and sunglasses

Other Information

protect the product in this container from excessive heat and direct sun.

Inactive Ingredients

Inactive Ingredients: Water(Aqua), Cyclomethicone, Caprylic/Capric Triglyceride, Arbutin, Mineral Oil, Talc, Methylparaben, Propylparaben, Phenyltrimethicone, Disodium Edta, Adenosine, Caviar Extract, Algae Extract, Dimethicone, Rosa Rubiginosa Seed Oil, Simmondsia Chinensis (Jojoba) Seed Oil, Squalane, Hydrolyzed Collagen, Macadamia Ternifolia Seed Oil, Rosmarinus Officinalis(Rosemary) Leaf Extract, Chamomilla Recutita (Matricaria) Flower Extract, Sodium Hyaluronate, Fagus Sylvatica Bud Extract, Ceramide 3, Beeswax (Cera Alba), Cetyl Peg/Ppg-10/1 Dimethicone, Dimethicone Copolyol, Polyethylene, Glycerin, Propylene Glycol, Sodium Chloride, Iron Oxides (Yellow), Iron Oxides (Red), Iron Oxides (Black), Fragrance, Hydroxyisohexyl 3-Cyclohexene Carboxaldehyde, Butylphenyl Methylpropional, Benzyl Salicylate, Hydroxycitronellal, Alpha - Isomethyl Lonone, Hexyl Cinnamal, Linalool, Citronellol

Questions or Comments?

visit www.misshaus.com or call 1-888-985-9887(Ext 104)

Warnings:
Do not use on damaged or broken skin.
When using this product, keep out of eyes. Rinse with water to Remove.
Stop use and ask a doctor, if rash ocurs.

Keep out of reach of children.